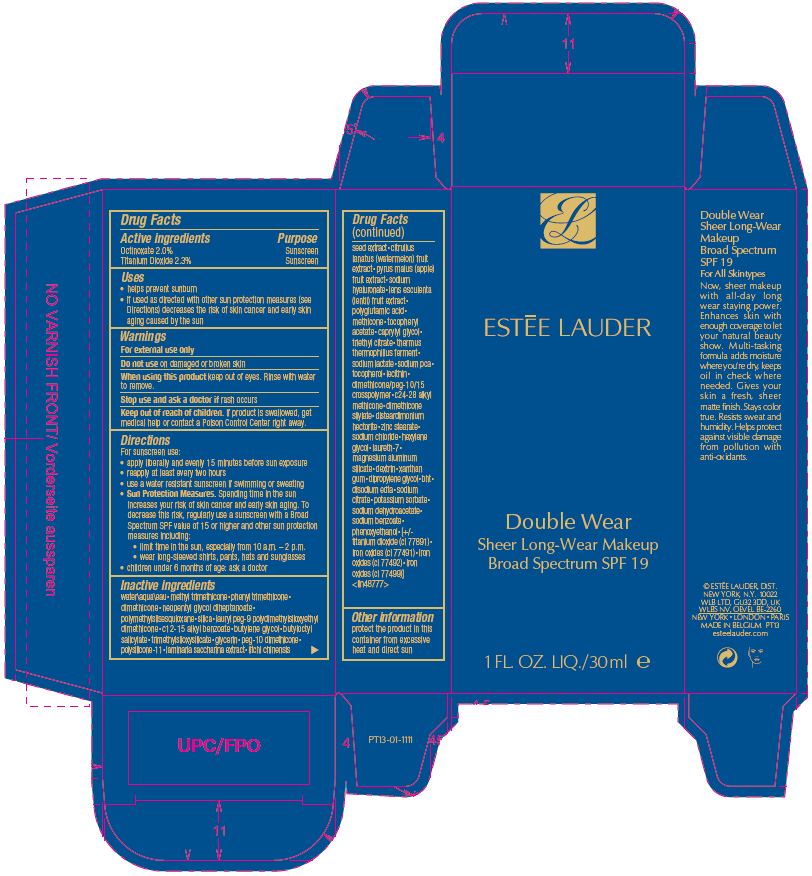 DRUG LABEL: ESTEE LAUDER DOUBLE WEAR SHEER LONG-WEAR MAKEUP BROAD SPECTRUM SPF 19
NDC: 11559-061 | Form: LIQUID
Manufacturer: ESTEE LAUDER INC
Category: otc | Type: HUMAN OTC DRUG LABEL
Date: 20241225

ACTIVE INGREDIENTS: OCTINOXATE 20 mg/1 mL; TITANIUM DIOXIDE 23 mg/1 mL
INACTIVE INGREDIENTS: WATER; METHYL TRIMETHICONE; PHENYL TRIMETHICONE; DIMETHICONE; NEOPENTYL GLYCOL DIHEPTANOATE; POLYMETHYLSILSESQUIOXANE (11 MICRONS); SILICA DIMETHYL SILYLATE; LAURYL PEG-9 POLYDIMETHYLSILOXYETHYL DIMETHICONE; ALKYL (C12-15) BENZOATE; BUTYLENE GLYCOL; BUTYLOCTYL SALICYLATE; TRIMETHYLSILOXYSILICATE (M/Q 0.6-0.8); GLYCERIN; SODIUM LACTATE; PEG-10 DIMETHICONE (600 CST); DIMETHICONE/VINYL DIMETHICONE CROSSPOLYMER (SOFT PARTICLE); SACCHARINA LATISSIMA; LITCHI CHINENSIS SEED; WATERMELON; APPLE; HYALURONATE SODIUM; LENS CULINARIS FRUIT; PACLITAXEL POLIGLUMEX; METHICONE (20 CST); .ALPHA.-TOCOPHEROL ACETATE; CAPRYLYL GLYCOL; SODIUM PYRROLIDONE CARBOXYLATE; TOCOPHEROL; LECITHIN, SOYBEAN; DIMETHICONE/PEG-10/15 CROSSPOLYMER; C24-28 OLEFIN; C30-45 ALKYL METHICONE; DISTEARDIMONIUM HECTORITE; ZINC STEARATE; SODIUM CHLORIDE; HEXYLENE GLYCOL; XANTHAN GUM; LAURETH-7; MAGNESIUM ALUMINUM SILICATE; DEXTRIN PALMITATE (CORN; 20000 MW); DIPROPYLENE GLYCOL; BUTYLATED HYDROXYTOLUENE; EDETATE DISODIUM; SODIUM CITRATE, UNSPECIFIED FORM; POTASSIUM SORBATE; SODIUM DEHYDROACETATE; SODIUM BENZOATE; PHENOXYETHANOL; FERRIC OXIDE RED; FERRIC OXIDE YELLOW; FERROSOFERRIC OXIDE; TRIETHYL CITRATE; THERMUS THERMOPHILUS

ESTEE LAUDER DOUBLE WEAR SHEER LONG-WEAR MAKEUP BROAD SPECTRUM SPF 19

Drug Facts

ACTIVE INGREDIENT

Active ingredients | Purpose
Octinoxate 2.0% | Sunscreen
Titanium Dioxide 2.3% | Sunscreen

Uses

- helps prevent sunburn
- if used as directed with other sun protection measures (see Directions) decreases the risk of skin cancer and early skin aging caused by the sun

Warnings

For external use only

Do not use on damaged or broken skin

When using this product keep out of eyes. Rinse with water to remove.

Stop use and ask a doctor if rash occurs

Keep out of reach of children. If product is swallowed, get medical help or contact a Poison Control Center right away.

Directions

For sunscreen use:

- apply liberally and evenly 15 minutes before sun exposure
- reapply at least every two hours
- use a water resistant sunscreen if swimming or sweating
- Sun Protection Measures. Spending time in the sun increases your risk of skin cancer and early skin aging. To decrease this risk, regularly use a sunscreen with a Broad Spectrum SPF value of 15 or higher and other sun protection measures including:
  - limit time in the sun, especially from 10 a.m. – 2 p.m.
  - wear long-sleeved shirts, pants, hats and sunglasses
- children under 6 months of age: ask a doctor

Inactive ingredients

water\aqua\eau • methyl trimethicone • phenyl trimethicone • dimethicone • neopentyl glycol diheptanoate • polymethylsilsesquioxane • silica • lauryl peg-9 polydimethylsiloxyethyl dimethicone • c12-15 alkyl benzoate • butylene glycol • butyloctyl salicylate • trimethylsiloxysilicate • glycerin • peg-10 dimethicone • polysilicone-11 • laminaria saccharina extract • litchi chinensis seed extract • citrullus lanatus (watermelon) fruit extract • pyrus malus (apple) fruit extract • sodium hyaluronate • lens esculenta (lentil) fruit extract • polyglutamic acid • methicone • tocopheryl acetate • caprylyl glycol • triethyl citrate • thermus thermophillus ferment • sodium lactate • sodium pca • tocopherol • lecithin • dimethicone/peg-10/15 crosspolymer • c24-28 alkyl methicone • dimethicone silylate • disteardimonium hectorite • zinc stearate • sodium chloride • hexylene glycol • laureth-7 • magnesium aluminum silicate • dextrin • xanthan gum • dipropylene glycol • bht • disodium edta • sodium citrate • potassium sorbate • sodium dehydroacetate • sodium benzoate • phenoxyethanol • [+/- titanium dioxide (ci 77891) • iron oxides (ci 77491) • iron oxides (ci 77492) • iron oxides (ci 77499)] <iln48777>

Other information

protect the product in this container from excessive heat and direct sun

PRINCIPAL DISPLAY PANEL - 30 ml Bottle Carton

ESTĒE LAUDER

Double Wear
Sheer Long-Wear Makeup
Broad Spectrum SPF 19

1 FL. OZ. LIQ. /30ml e